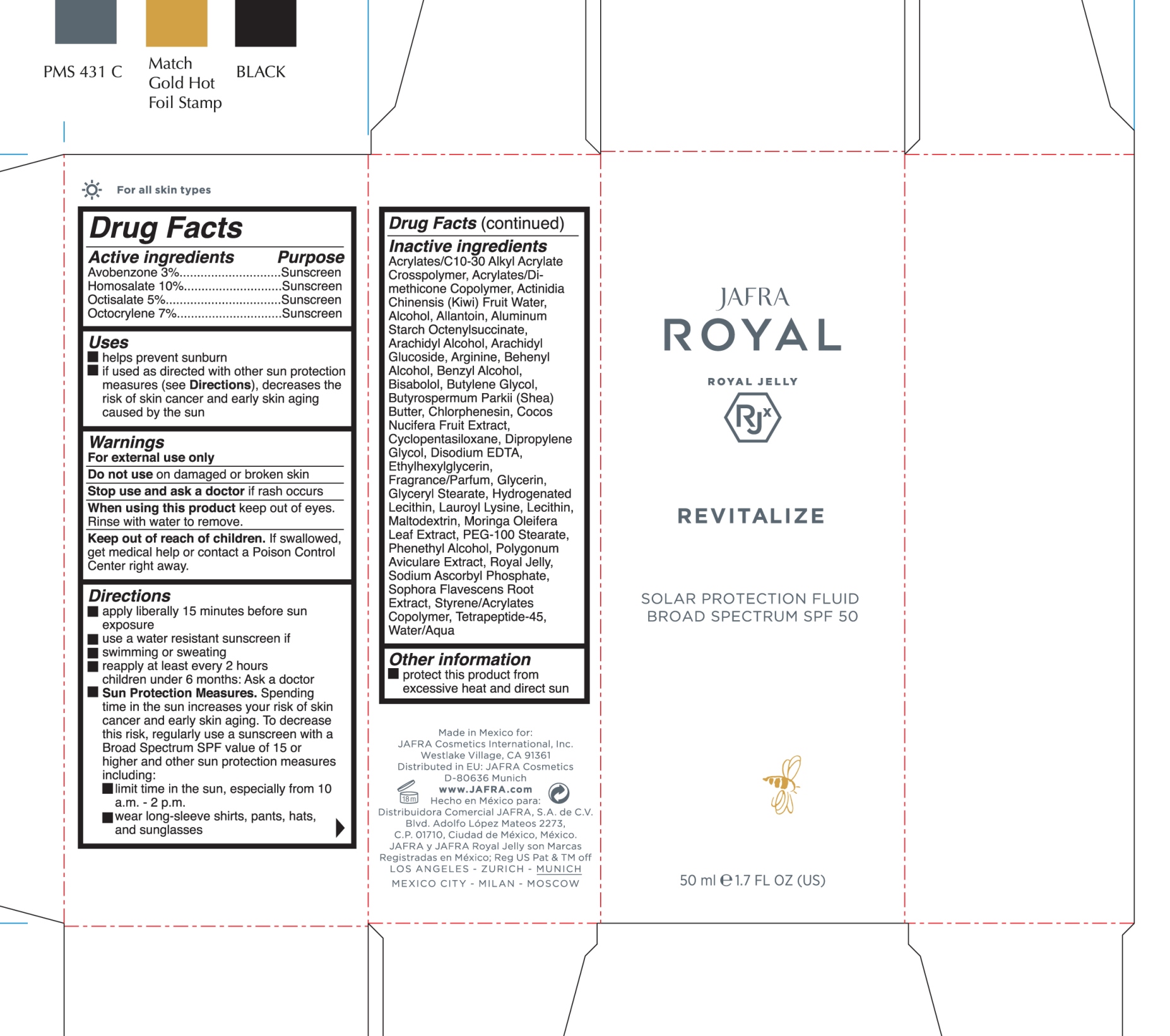 DRUG LABEL: Solar Protection Fluid Broad Spectrum SPF 50
NDC: 68828-282 | Form: CREAM
Manufacturer: JAFRA COSMETICS INTERNATIONAL
Category: otc | Type: HUMAN OTC DRUG LABEL
Date: 20200611

ACTIVE INGREDIENTS: AVOBENZONE 3 g/100 mL; HOMOSALATE 10 g/100 mL; OCTISALATE 5 g/100 mL; OCTOCRYLENE 7 g/100 mL
INACTIVE INGREDIENTS: CARBOMER INTERPOLYMER TYPE A (ALLYL SUCROSE CROSSLINKED); KIWI FRUIT OIL; ALCOHOL; ALLANTOIN; ALUMINUM STARCH OCTENYLSUCCINATE; ARACHIDYL ALCOHOL; ARACHIDYL GLUCOSIDE; ARGININE; DOCOSANOL; BENZYL ALCOHOL; LEVOMENOL; BUTYLENE GLYCOL; SHEA BUTTER; CHLORPHENESIN; COCONUT; CYCLOMETHICONE 5; DIPROPYLENE GLYCOL; EDETATE DISODIUM; ETHYLHEXYLGLYCERIN; GLYCERIN; GLYCERYL MONOSTEARATE; HYDROGENATED SOYBEAN LECITHIN; LAUROYL LYSINE; LECITHIN, SOYBEAN; MALTODEXTRIN; MORINGA OLEIFERA LEAF; PEG-100 STEARATE; PHENYLETHYL ALCOHOL; POLYGONUM AVICULARE TOP; ROYAL JELLY; SODIUM ASCORBYL PHOSPHATE; SOPHORA FLAVESCENS ROOT; WATER

Royal Jelly - Solar Protection Fluid Broad Spectrum SPF 50

Active Ingredients Purpose

Avobenzone 3% Sunscreen

Homosalate 10% Suncreen

Octisalate 5% Suncreen

Octocrylene 7% Sunscreen

Uses

- Helps prevent sunburn
- if used as directed with other sun protection measures (see Directions), decreases the risk of skin cancer and early skin aging caused by the sun

Keep out of reach of children. If swallowed, get medical help or contact a Poison Control Center right away

Stop use and ask a doctor if rash occurs

Warnings

- For external use only
- Do not use on damaged or broken skin
- when using this product keep out of eyes. Rinse with water to remove.

Directions

- apply liberally 15 minutes before sun exposure
- use a water resistant sunscreen if
- swimming or sweating
- reapply at least every 2 hours children under 6 months: Ask a doctor
- Sun Protection Measures. Spending time in the sun icreases your risk of skin cancer and early skin aging. To decrease this risk, regularly use a sunscreen with a Broad Specturm SPF 15 or higher and other sun protection measures including:
- limit time in the sun, especially from 10 a.m. - 2 p.m.
- Wear long-sleeve shirts, pants, hats, and sunglasses

Inactive ingredients

Acrylates/C10-30 Alkyl Acrylate Crosspolymer, Acrylates/Dimethicone Copolymer, Actinidia Chinensis (Kiwi) Fruit Water, Alcohol, Allantoin, Aluminum Starch Octenylsuccinate, Arachidyl Alcohol, Arachidyl Glucoside, Arginine, Behenyl Alcohol, Benzyl Alcohol, Bisabolol,
Butylene Glycol, Butyrospermum Parkii (Shea) Butter, Chlorphenesin, Cocos Nucifera Fruit Extract, Cyclopentasiloxane, Dipropylene Glycol, Disodium EDTA, Ethylhexylglycerin, Fragrance/Parfum, Glycerin, Glyceryl Stearate, Hydrogenated Lecithin, Lauroyl Lysine, Lecithin, Maltodextrin, Moringa Oleifera Leaf Extract, PEG-100 Stearate, Phenethyl Alcohol, Polygonum Aviculare Extract, Royal Jelly, Sodium Ascorbyl Phosphate, Sophora Flavescens Root Extract, Styrene/Acrylate Copolymer, Tetrapeptide-45, Water/Aqua

PACKAGE LABEL

JAFRA

Royal Jelly

Solar Protection Fluid

Broad Spectrum SPF 50

50 ml 1.7 FL OZ (US)